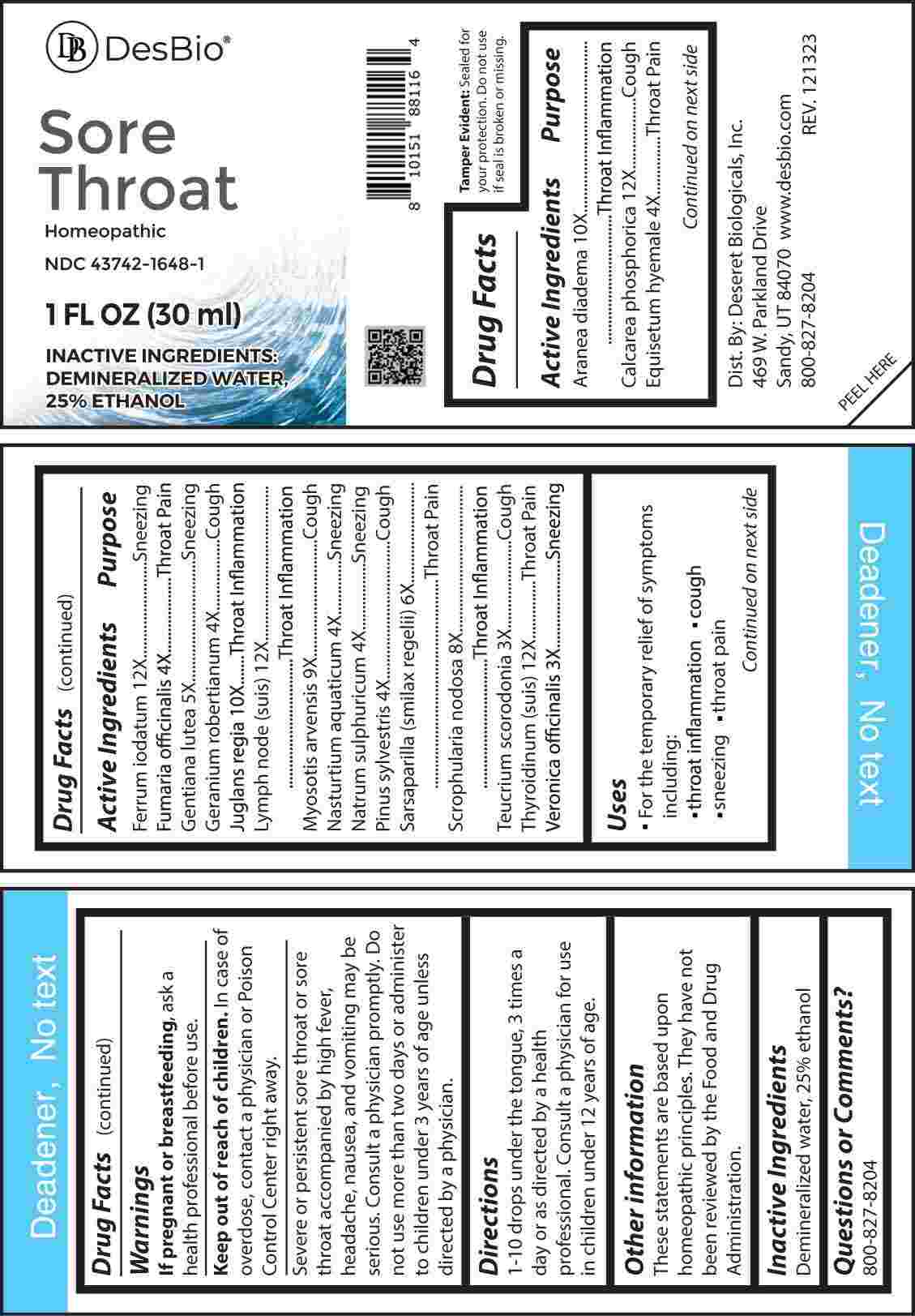 DRUG LABEL: Sore Throat
NDC: 43742-1648 | Form: LIQUID
Manufacturer: Deseret Biologicals, Inc.
Category: homeopathic | Type: HUMAN OTC DRUG LABEL
Date: 20240402

ACTIVE INGREDIENTS: TEUCRIUM SCORODONIA FLOWERING TOP 3 [hp_X]/1 mL; VERONICA OFFICINALIS FLOWERING TOP 3 [hp_X]/1 mL; EQUISETUM HYEMALE WHOLE 4 [hp_X]/1 mL; FUMARIA OFFICINALIS FLOWERING TOP 4 [hp_X]/1 mL; GERANIUM ROBERTIANUM WHOLE 4 [hp_X]/1 mL; NASTURTIUM OFFICINALE 4 [hp_X]/1 mL; SODIUM SULFATE 4 [hp_X]/1 mL; PINUS SYLVESTRIS LEAFY TWIG 4 [hp_X]/1 mL; GENTIANA LUTEA ROOT 5 [hp_X]/1 mL; SMILAX ORNATA ROOT 6 [hp_X]/1 mL; SCROPHULARIA NODOSA WHOLE 8 [hp_X]/1 mL; MYOSOTIS ARVENSIS WHOLE 9 [hp_X]/1 mL; ARANEUS DIADEMATUS 10 [hp_X]/1 mL; JUGLANS REGIA LEAF 10 [hp_X]/1 mL; JUGLANS REGIA FRUIT RIND, IMMATURE 10 [hp_X]/1 mL; TRIBASIC CALCIUM PHOSPHATE 12 [hp_X]/1 mL; FERROUS IODIDE 12 [hp_X]/1 mL; SUS SCROFA LYMPH 12 [hp_X]/1 mL; THYROID 12 [hp_X]/1 mL
INACTIVE INGREDIENTS: WATER; ALCOHOL

DRUG FACTS:

ACTIVE INGREDIENTS:

Aranea Diadema 10X, Calcarea Phosphorica 12X, Equisetum Hyemale 4X, Ferrum Iodatum 12X, Fumaria Officinalis 4X, Gentiana Lutea 5X, Geranium Robertianum 4X, Juglans Regia 10X, Lymph Node (Suis) 12X, Myosotis Arvensis 9X, Nasturtium Aquaticum 4X, Natrum Sulphuricum 4X, Pinus Sylvestris 4X, Sarsaparilla (Smilax Regelii) 6X, Scrophularia Nodosa 8X, Teucrium Scorodonia 3X, Thyroidinum (Suis) 12X, Veronica Officinalis 3X.

PURPOSE:

Aranea Diadema – Throat Inflammation, Calcarea Phosphorica - Cough, Equisetum Hyemale – Throat Pain, Ferrum Iodatum - Sneezing, Fumaria Officinalis – Throat Pain, Gentiana Lutea - Sneezing, Geranium Robertianum - Cough, Juglans Regia – Throat Inflammation, Lymph Node (Suis) – Throat Inflammation, Myosotis Arvensis - Cough, Nasturtium Aquaticum - Sneezing, Natrum Sulphuricum - Sneezing, Pinus Sylvestris - Cough, Sarsaparilla (Smilax Regelii) – Throat Pain, Scrophularia Nodosa – Throat Inflammation, Teucrium Scorodonia - Cough, Thyroidinum (Suis) – Throat Pain, Veronica Officinalis - Sneezing

USES:

• For the temporary relief of symptoms including:

• throat inflammation • cough • sneezing • throat pain

These statements are based upon homeopathic principles. They have not been reviewed by the Food and Drug Administration.

WARNINGS:

If pregnant or breast-feeding, ask a health professional before use.

Keep out of reach of children. In case of overdose, contact a physician or Poison Control Center right away.

Severe or persistent sore throat or sore throat accompanied by high fever, headache, nausea, and vomiting may be serious. Consult a physician promptly. Do not use more than two days or administer to children under 3 years of age unless directed by a physician.

Tamper Evident: Sealed for your protection. Do not use if seal is broken or missing.

KEEP OUT OF REACH OF CHILDREN:

In case of overdose, contact a physician or Poison Control Center right away.

DIRECTIONS:

1-10 drops under the tongue, 3 times a day or as directed by a health professional. Consult a physician for use in children under 12 years of age.

INACTIVE INGREDIENTS:

Demineralized water, 25% ethanol

QUESTIONS:

Dist. By: Deseret Biologicals, Inc.
469 W. Parkland Drive
Sandy, UT 84070

www.desbio.com

800-827-8204

PACKAGE LABEL DISPLAY:

Des Bio

Sore Throat

Homeopathic

NDC 43742-1648-1

1 FL OZ (30 ml)